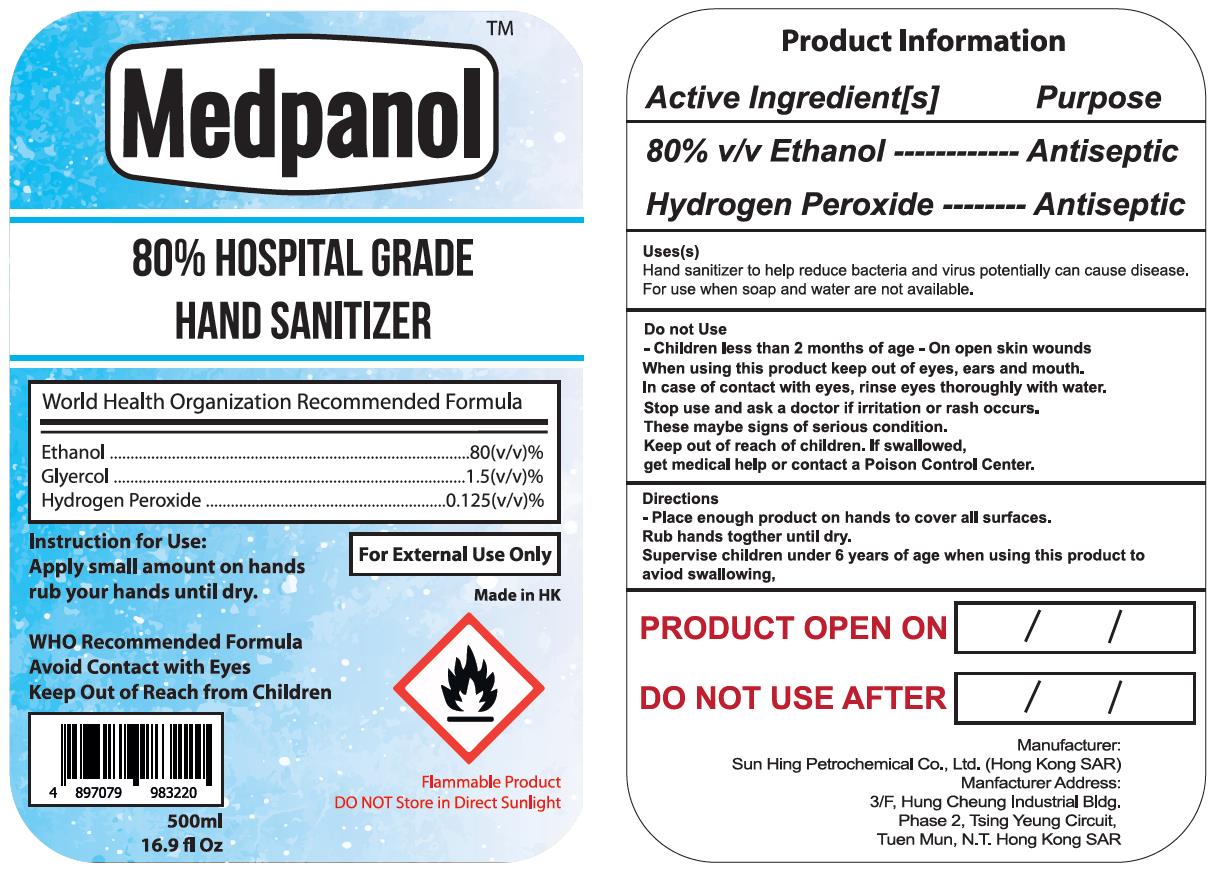 DRUG LABEL: Medpanol
NDC: 77606-101 | Form: GEL
Manufacturer: Sun Hing Petrochemical Company Limited
Category: otc | Type: HUMAN OTC DRUG LABEL
Date: 20200518

ACTIVE INGREDIENTS: ALCOHOL 400 mL/500 mL
INACTIVE INGREDIENTS: GLYCERIN; WATER; HYDROGEN PEROXIDE

SunHing, Medpanol Hand Sanitizer, Ethanol 80% v/v, Gel, Bottle-Pump, 500mL

Active Ingredient(s)

Ethanol 80% v/v. Purpose: Antiseptic

Purpose

Antiseptic.

Use

Hand sanitizer to help reduce bacteria and virus potentially can cause disease.
For use when soap and water are not available.

Warnings

For external use only. Flammable. Keep away from heat or flame.

Do not use

- Children less than 2 months of age

- On open skin wounds

When using this product keep out of eyes, ears and mouth. In case of contact with eyes, rinse eyes thoroughly with water.

Stop use and ask a doctor if irritation or rash occurs. These maybe signs of serious condition.

Keep out of reach of children. If swallowed, get medical help or contact a Poison Control Center.

Directions

Place enough product on hands to cover all surfaces. Rub hands togther until dry.
Supervise children under 6 years of age when using this product to aviod swallowing.

Other information

DO NOT Store in Direct Sunlight.

Inactive ingredients

Water, Glycerin, Hydrogen Peroxide.